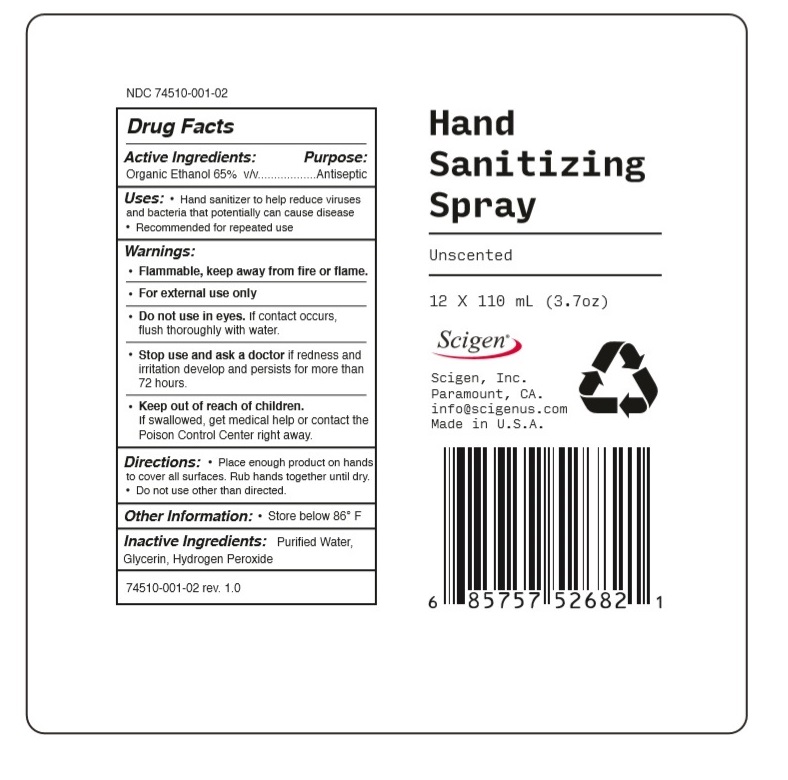 DRUG LABEL: Scigen Hand Sanitizer
NDC: 74510-001 | Form: SPRAY
Manufacturer: Scigen, Inc
Category: otc | Type: HUMAN OTC DRUG LABEL
Date: 20201123

ACTIVE INGREDIENTS: ALCOHOL 65 mL/100 mL
INACTIVE INGREDIENTS: WATER; GLYCERIN; HYDROGEN PEROXIDE

Scigen Hand Sanitizer

Active Ingredients:

Organic Ethanol 65% v/v

Purpose:

Antiseptic

INDICATIONS AND USAGE

Uses: • Hand sanitizer to help reduce viruses and bacteria that potentially can cause disease • Recommended for repeated use

Warnings:

- Flammable, keep away from fire or flame.
- For external use only
- Do not use in eyes. If contact occurs, flush thoroughly with water.
- Stop use and ask a doctor if redness and irritation develop and persists for more than 72 hours.

Keep out of reach of children. If swallowed, get medical help or contact the Poison Control Center right away.

DOSAGE AND ADMINISTRATION

Directions: • Place enough product on hands to cover all surfaces. Rub hands together until dry • Do not use other than directed.

Other Information: • Store below 86° F

Inactive Ingredients: Purified Water, Glycerin, Hydrogen Peroxide

Unscented

Scigen, Inc.

Paramount, CA.

info@scigenus.com

Made in U.S.A.